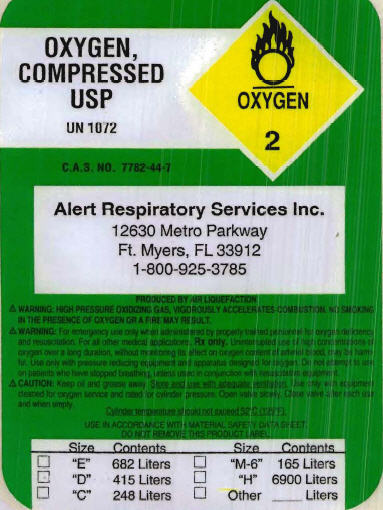 DRUG LABEL: Oxygen
NDC: 63054-0123 | Form: GAS
Manufacturer: Alert Respiratory Services, Inc.
Category: prescription | Type: HUMAN PRESCRIPTION DRUG LABEL
Date: 20110706

ACTIVE INGREDIENTS: OXYGEN 99 L/100 L

Oxygen, Compressed

PACKAGE/LABEL PRINCIPAL DISPLAY PANEL

OXYGEN, COMPRESSED USP

UN 1072

C.A.S. No. 7782-44-7

Alert Respiratory Services Inc.

12630 Metro Parkway

Ft. Myers, FL 33912

1-800-925-3785

PRODUCED BY AIR LIQUEFACTION

WARNING: HIGH PRESSURE OXIDIZING GAS, VIGOROUSLY ACCELERATES COMBUSTION. NO SMOKING IN THE PRESENCE OF OXYGEN OR A FIRE MAY RESULT.

WARNING: For emergency use only when administrated by properly trained personnel for oxygen deficiency and resuscitation. For all other medical applications, Rx only. Uninterrupted use of high concentrations of oxygen over a long duration, without monitoring its effect on oxygen content of arterial blood, may be harmful. Use only with pressure reducing equipment and apparatus designed for oxygen. Do not attempt to use on patients who have stopped breathing, unless used in conjunction with resuscitative equipment.

CAUTION: Keep oil and grease away. Store and use with adequate ventilation. Use only with equipment cleaned for oxygen service and rated for cylinder pressure. Open valve slowly. Close valve after each use and when empty.

Cylinder temperature should not exceed 52°C (125°F).

USE IN ACCORDANCE WITH MATERIAL SAFETY DATA SHEET.

DO NOT REMOVE THIS PRODUCT LABEL.

Label